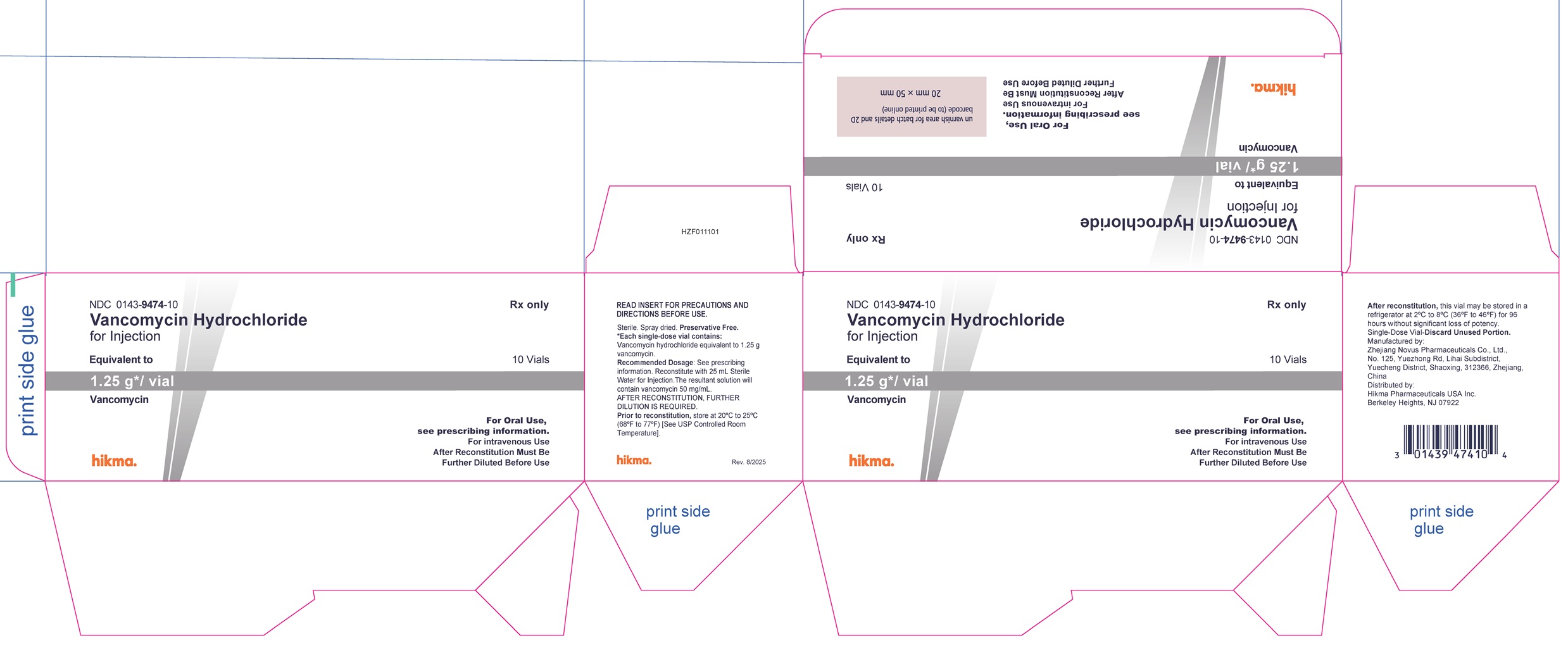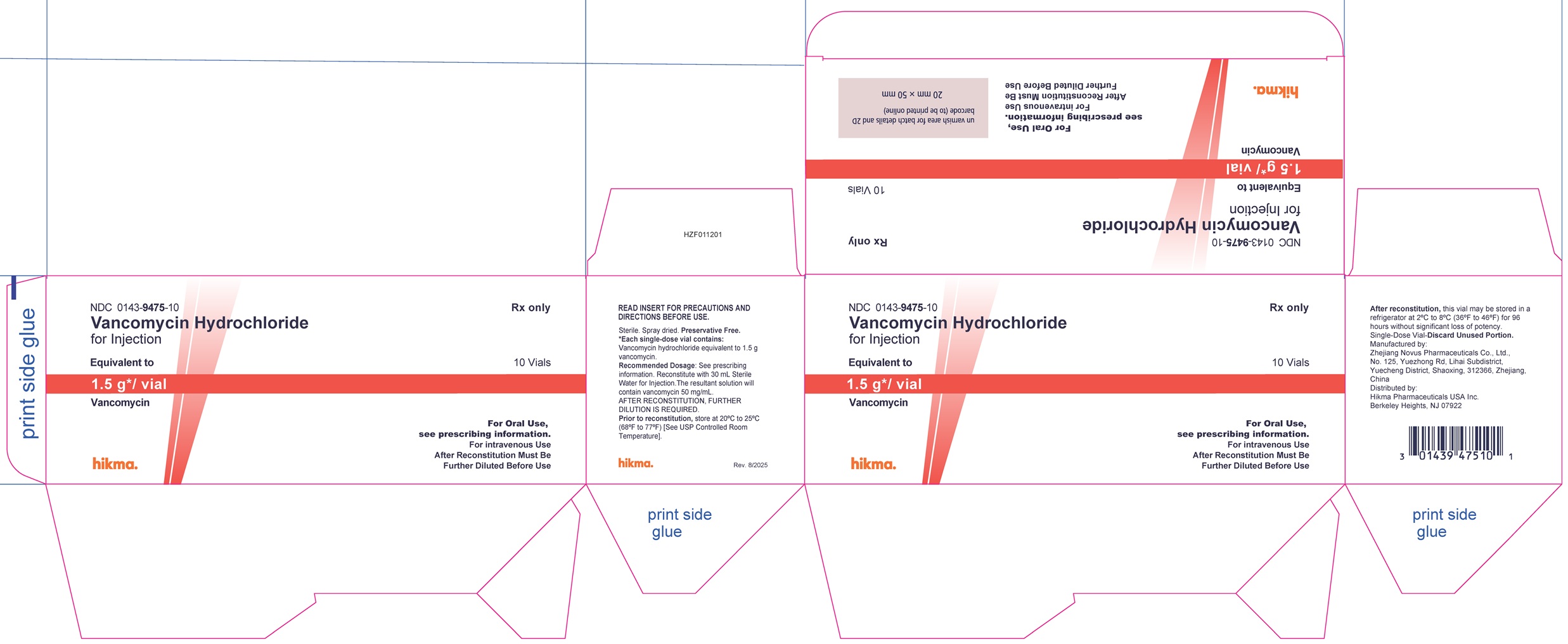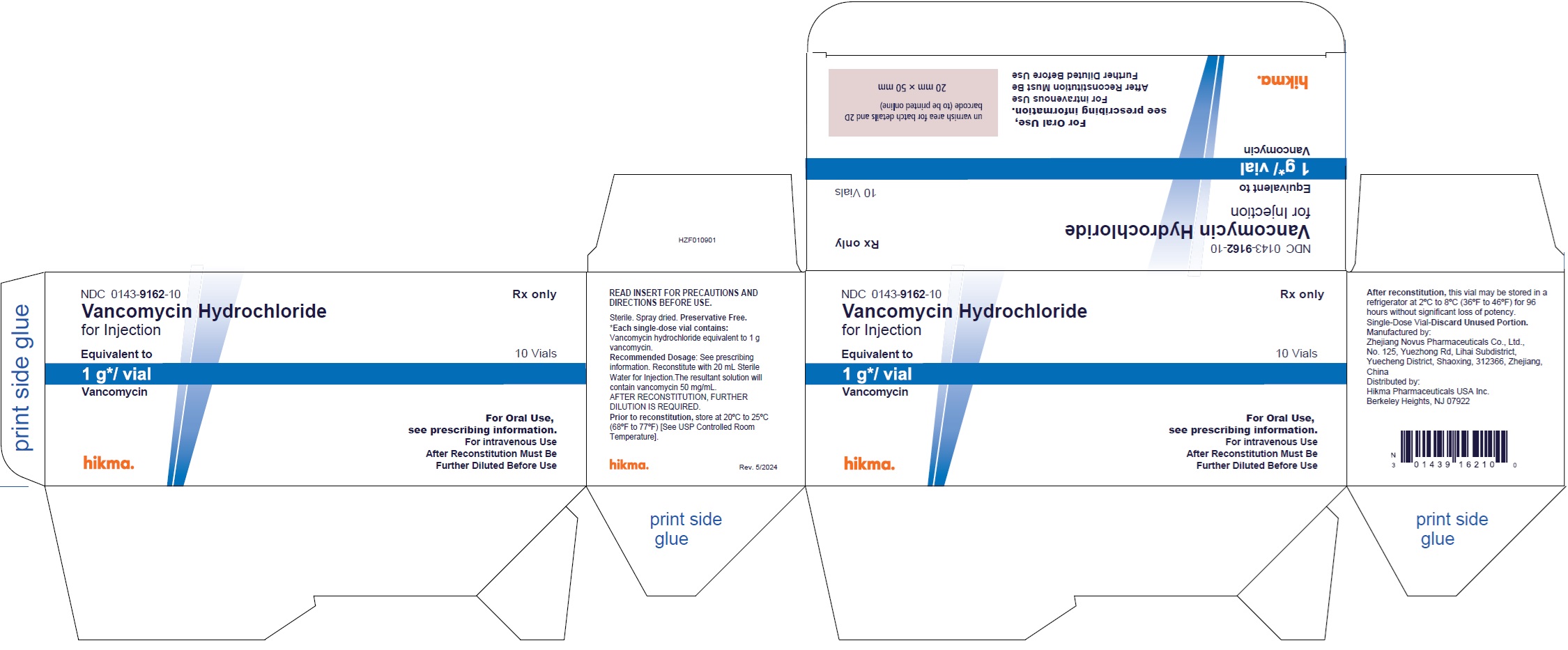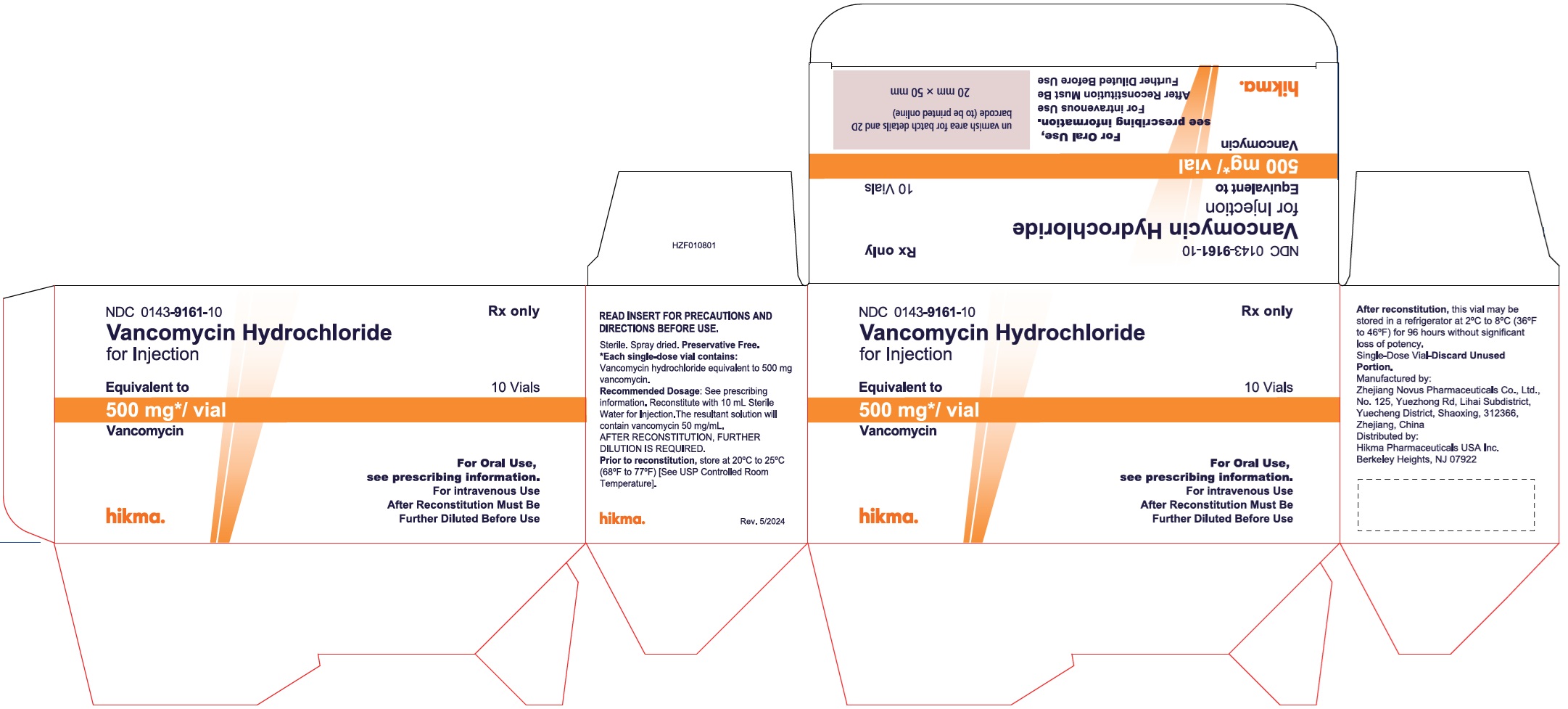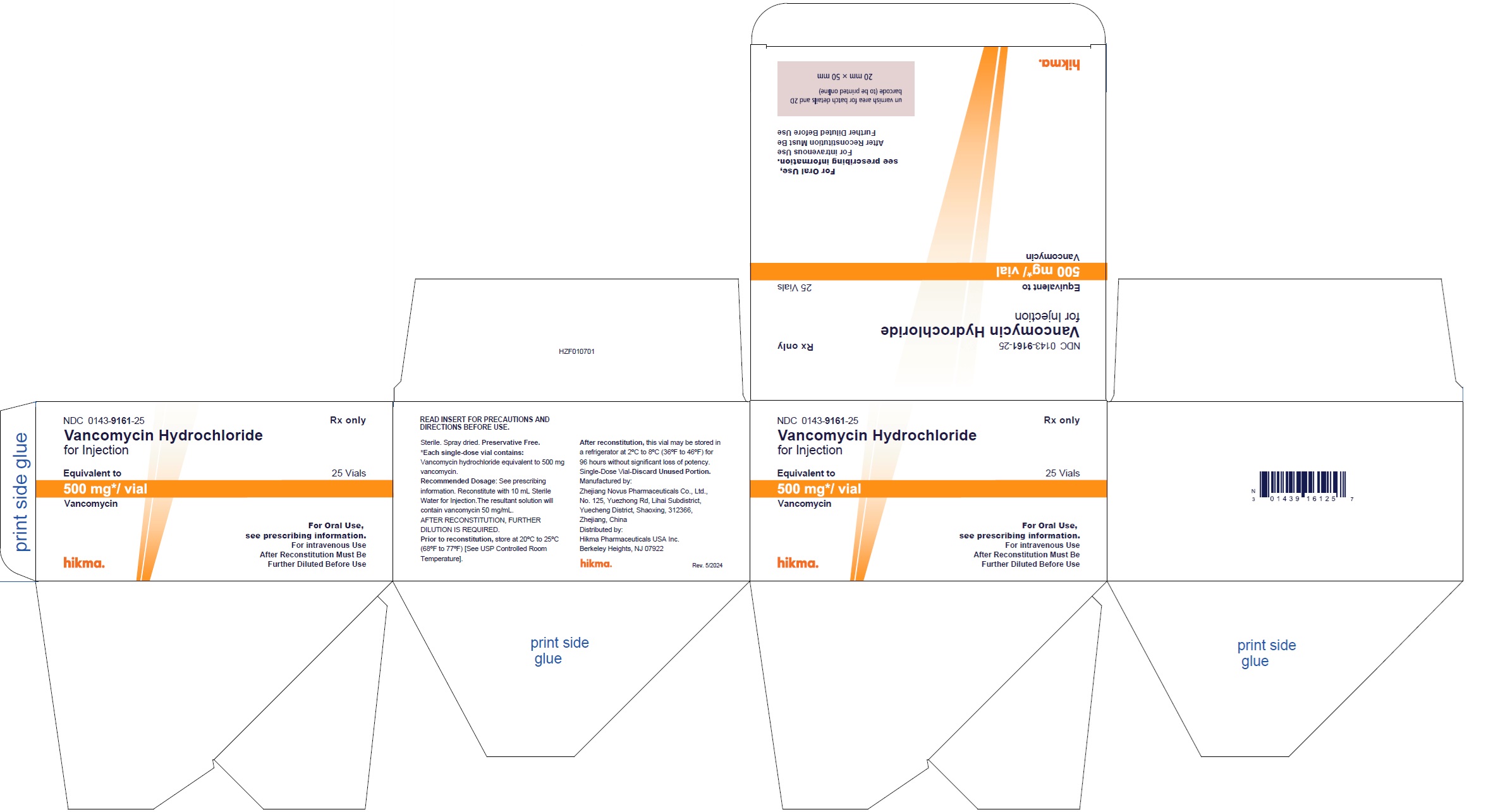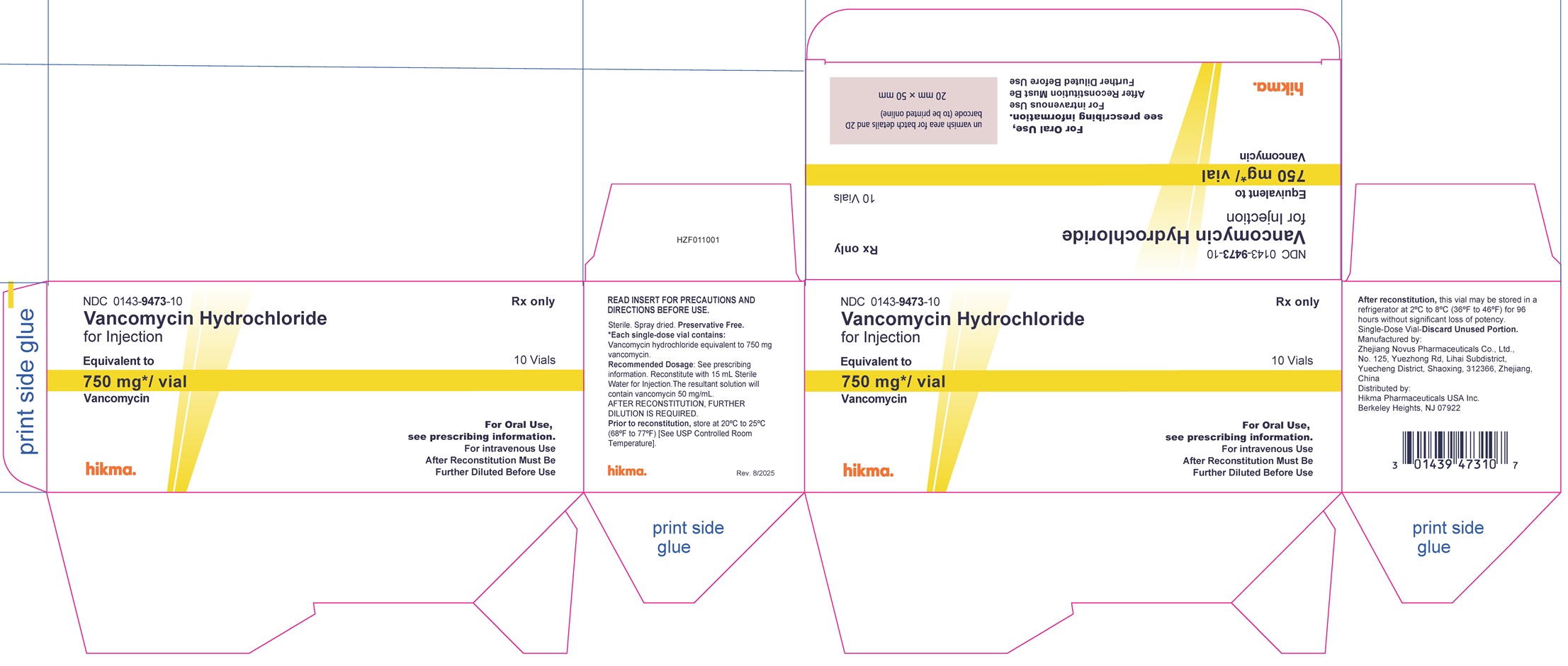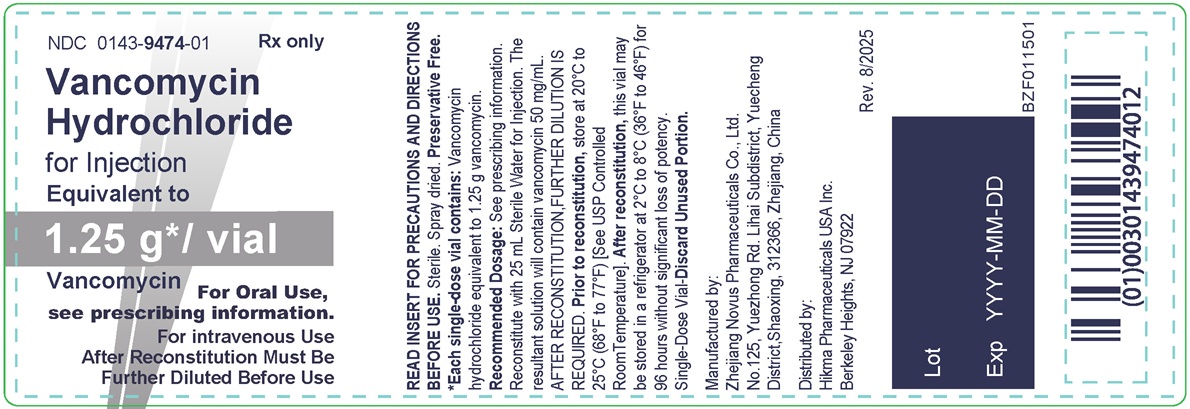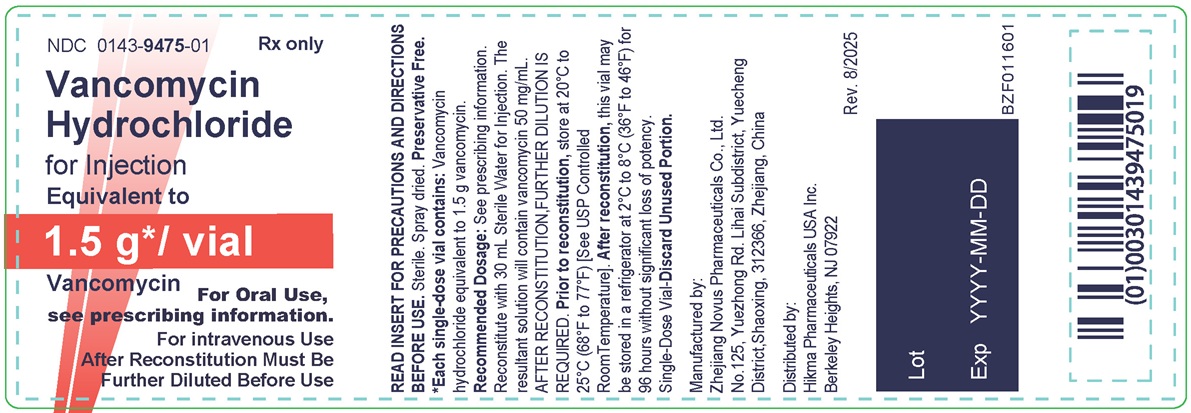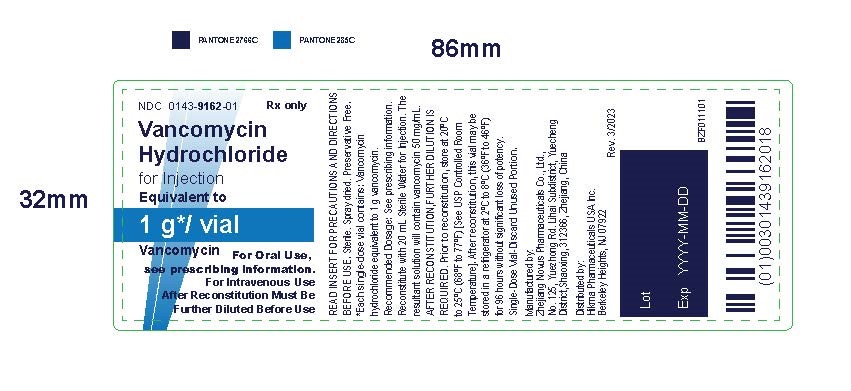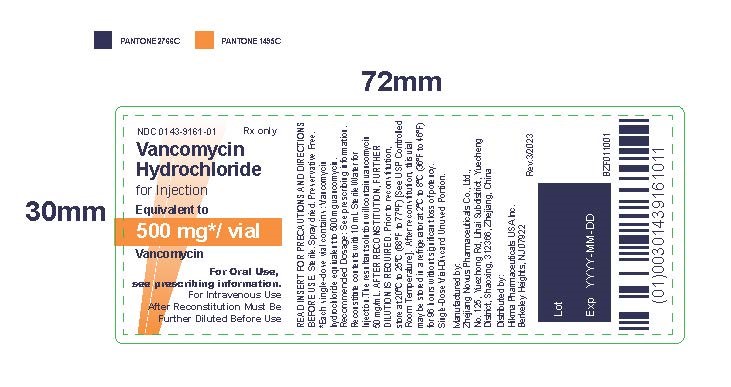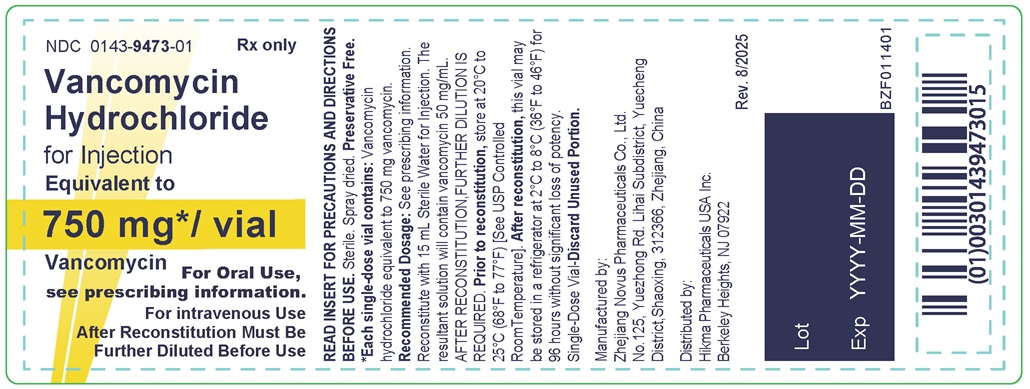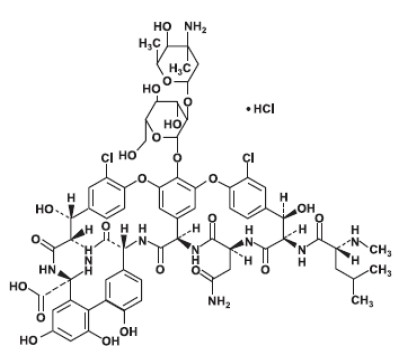 DRUG LABEL: VANCOMYCIN HYDROCHLORIDE
NDC: 0143-9161 | Form: INJECTION, POWDER, FOR SOLUTION
Manufacturer: HIKMA PHARMACEUTICALS USA INC.
Category: prescription | Type: HUMAN PRESCRIPTION DRUG LABEL
Date: 20250813

ACTIVE INGREDIENTS: VANCOMYCIN HYDROCHLORIDE 513 mg/1 mg
INACTIVE INGREDIENTS: TREHALOSE 125 mg/1 mg; POLYSORBATE 80 0.05 mg/1 mg; HYDROCHLORIC ACID

HIGHLIGHTS OF PRESCRIBING INFORMATION

These highlights do not include all the information needed to use VANCOMYCIN HYDROCHLORIDE FOR INJECTION safely and effectively. See full prescribing information for VANCOMYCIN HYDROCHLORIDE FOR INJECTION.
VANCOMYCIN HYDROCHLORIDE for injection, for intravenous use or oral use
Initial U.S. Approval: 1958

1 INDICATIONS AND USAGE

Vancomycin Hydrochloride for Injection is a glycopeptide antibacterial indicated in adult and pediatric patients less than 18 years of age as follows:

- Vancomycin Hydrochloride for Injection administered intravenously is indicated for the treatment of:

o Septicemia (1.1)
o Infective Endocarditis (1.2)
o Skin and Skin Structure Infections (1.3)
o Bone Infections (1.4)
o Lower Respiratory Tract Infections (1.5)

- Vancomycin Hydrochloride for Injection administered orally is indicated for the treatment of:

o Clostridioides difficile-associated diarrhea (1.6)
o Enterocolitis caused by Staphylococcus aureus (including methicillin-resistant strains) (1.7)

Limitations of Use (1.8)

- Vancomycin Hydrochloride for Injection administered intravenously is not approved for the treatment of C. difficile-associated diarrhea and enterocolitis caused by susceptible isolates of Staphylococcus aureus because it is not effective.
- Vancomycin Hydrochloride for Injection administered orally is not approved for the treatment of septicemia, infective endocarditis, skin and skin structure infections, bone infections and lower respiratory tract infections because it is not effective.

To reduce the development of drug-resistant bacteria and maintain the effectiveness of Vancomycin Hydrochloride for Injection and other antibacterial drugs, Vancomycin Hydrochloride for Injection should be used only to treat or prevent infections that are proven or strongly suspected to be caused by susceptible bacteria. (1.9)

2 DOSAGE AND ADMINISTRATION

See full prescribing information for important information on intravenous and oral administration, preparation and storage instructions (2.1, 2.5, 2.8).

Recommended Dosage and Administration

- Intravenous Use:

o Administer Vancomycin Hydrochloride for Injection in a diluted solution by intravenous infusion over 60 minutes or greater to reduce the risk of infusion reactions.
o Adult Patients: 2 grams (g) divided either as 0.5 g every 6 hours or 1 g every 12 hours (2.2)
o Pediatric Patients (1 month and older): 10 mg/kg per dose given every 6 hours (2.2)
o Pediatric Patients (younger than 1 month of age): See full prescribing information for recommended dosage (2.2)
o Patients with Renal Impairment: See full prescribing information for recommended dosage in patients with renal impairment (2.4)

- Oral use:

Adult Patients (18 years of age or greater):

o C. difficile-Associated Diarrhea: 125 mg administered orally 4 times daily for 10 days (2.3).
o Staphylococcal enterocolitis: 500 mg to 2 grams administered orally in 3 or 4 divided doses for 7 to 10 days (2.3)

Pediatric Patients (less than 18 years of age):
o For both C. difficile-associated diarrhea and staphylococcal enterocolitis: 40 mg/kg in 3 or 4 divided doses for 7 days to 10 days. The total daily dosage should not exceed 2 g (2.3)

3 DOSAGE FORMS AND STRENGTHS

Vancomycin Hydrochloride for Injection is a sterile spray-dried powder for injection in single-dose vials containing vancomycin hydrochloride equivalent to 500 mg, 750 mg, 1 gram, 1.25 gram or 1.5 gram of vancomycin base (3)

4 CONTRAINDICATIONS

Hypersensitivity to vancomycin, and polysorbate 80 (4)

5 WARNINGS AND PRECAUTIONS

- Nephrotoxicity: Systemic vancomycin exposure may result in acute kidney injury (AKI) including acute renal failure, mainly due to interstitial nephritis or less commonly acute tubular necrosis. Monitor serum vancomycin concentrations and renal function in patients receiving Vancomycin Hydrochloride for Injection intravenously. Monitor renal function in patients over 65 years of age receiving Vancomycin Hydrochloride for Injection orally. (5.1)
- Ototoxicity: Ototoxicity has occurred in patients administered vancomycin intravenously or orally. Monitor for signs and symptoms of ototoxicity during oral or intravenous therapy. Assessment of auditory function may be appropriate in some instances. (5.2)
- Severe Dermatologic Reactions: Discontinue Vancomycin Hydrochloride for Injection at the first appearance of skin rashes, mucosal lesions, or blisters (5.3).
- Neutropenia: This has been reported in patients administered vancomycin intravenously or orally. Periodically monitor leukocyte count. (5.4)
- Infusion Reactions: Hypotension, including shock and cardiac arrest, wheezing, dyspnea, urticaria, muscular, chest pain and vancomycin infusion reaction which manifests as pruritus and erythema that involves the face, neck and upper torso may occur with rapid intravenous administration. To reduce the risk of infusion reactions, administer Vancomycin Hydrochloride for Injection in a diluted solution over a period of 60 minutes or greater and also prior to intravenous anesthetic agents. (2.1, 5.5)
- Phlebitis: To reduce the risk of local irritation and phlebitis, administer Vancomycin Hydrochloride for Injection by a secure intravenous route of administration. (5.6)
- Clostridioides difficile-Associated Diarrhea: Evaluate patients if diarrhea occurs. (5.7)
- Development of Drug-Resistant Bacteria: Prescribing Vancomycin Hydrochloride for Injection in the absence of a proven or strongly suspected bacterial infection is unlikely to provide benefit to the patient and increases the risk of the development of drug resistant bacteria. (5.9)

6 ADVERSE REACTIONS

The common adverse reactions following intravenously, and orally administered vancomycin were acute kidney injury, hearing loss, neutropenia, anaphylaxis, vancomycin infusion reaction. (6.1)
The most common adverse reactions of orally administered vancomycin (> 10%) were nausea, abdominal pain, and hypokalemia (6.1).

To report SUSPECTED ADVERSE REACTIONS, contact Hikma Injectables USA Inc.at 1-877-845-0689 or FDA at 1-800-FDA-1088 or www.fda.gov/medwatch.

7 DRUG INTERACTIONS

- Anesthetic Agents: Concomitant administration of vancomycin and anesthetic agents has been associated with erythema and histamine-like flushing. (2.1, 7.1)
- Piperacillin/Tazobactam: Increased incidence of acute kidney injury in patients administered concomitant piperacillin/tazobactam and vancomycin as compared to vancomycin alone. Monitor kidney function in patients (7.2)

FULL PRESCRIBING INFORMATION

1 INDICATIONS AND USAGE

1.1 Septicemia

Vancomycin Hydrochloride for Injection administered intravenously is indicated in adults and pediatric patients less than 18 years of age for the treatment of septicemia due to:

- Susceptible isolates of methicillin-resistant Staphylococcus aureus (MRSA) and coagulase negative staphylococci.
- Methicillin-susceptible staphylococci in penicillin-allergic patients, or those patients who cannot receive or who have failed to respond to other drugs, including penicillins or cephalosporins.

1.2 Infective Endocarditis

Vancomycin Hydrochloride for Injection administered intravenously is indicated in adults and pediatric patients less than 18 years of age for the treatment of infective endocarditis due to:

- Susceptible isolates of MRSA.
- Viridans group streptococci Streptococcus gallolyticus (previously known as Streptococcus bovis), Enterococcus species and Corynebacterium species. For enterococcal endocarditis, use Vancomycin Hydrochloride for Injection in combination with an aminoglycoside.
- Methicillin-susceptible staphylococci in penicillin-allergic patients, or those patients who cannot receive or who have failed to respond to other drugs, including penicillins or cephalosporins.

Vancomycin Hydrochloride for Injection administered intravenously is indicated in adults and pediatric patients less than 18 years of age for the treatment of early-onset prosthetic valve endocarditis caused by Staphylococcus epidermidis in combination with rifampin and an aminoglycoside.

1.3 Skin and Skin Structure Infections

Vancomycin Hydrochloride for Injection administered intravenously is indicated in adults and pediatric patients less than 18 years of age for the treatment of skin and skin structure infections due to:

- Susceptible isolates of MRSA and coagulase negative staphylococci.
- Methicillin-susceptible staphylococci in penicillin-allergic patients, or those patients who cannot receive or who have failed to respond to other drugs, including penicillins or cephalosporins.

1.4 Bone Infections

Vancomycin Hydrochloride for Injection administered intravenously is indicated in adults and pediatric patients less than 18 years of age for the treatment of bone infections due to:

- Susceptible isolates of MRSA and coagulase negative staphylococci.
- Methicillin-susceptible staphylococci in penicillin-allergic patients, or those patients who cannot receive or who have failed to respond to other drugs, including penicillins or cephalosporins.

1.5 Lower Respiratory Tract Infections

Vancomycin Hydrochloride for Injection administered intravenously is indicated in adults and pediatric patients less than 18 years of age for the treatment of lower respiratory tract infections due to:

- Susceptible isolates of MRSA
- Methicillin-susceptible staphylococci in penicillin-allergic patients, or those patients who cannot receive or who have failed to respond to other drugs, including penicillins or cephalosporins.

1.6 Clostridioides difficile-Associated Diarrhea

Vancomycin Hydrochloride for Injection administered orally is indicated for the treatment of C. difficile-associated diarrhea (CDAD) in adult and pediatric patients less than 18 years of age.

1.7 Enterocolitis Caused by S. aureus (including methicillin-resistant strains)

Vancomycin Hydrochloride for Injection administered orally is indicated for the treatment of enterocolitis caused by susceptible isolates of Staphylococcus aureus in adults and pediatric patients less than 18 years of age.

1.8 Limitations of Use

Vancomycin Hydrochloride for Injection administered intravenously is not approved for the treatment of the following conditions because it is not effective:

- C. difficile-Associated Diarrhea
- Enterocolitis caused by susceptible isolates of Staphylococcus aureus

Vancomycin Hydrochloride for Injection administered orally is not approved for the treatment of the following conditions because it is not effective:

- Septicemia due to susceptible isolates of MRSA or methicillin-susceptible staphylococci
- Infective endocarditis due to susceptible isolates of MRSA, methicillin susceptible staphylococci, Viridans group streptococci Streptococcus gallolyticus, Enterococcus species and Corynebacterium species, or for the treatment of early-onset prosthetic valve endocarditis caused by Staphylococcus epidermidis in combination with rifampin and an aminoglycoside
- Skin and skin structure infections due to susceptible isolates of MRSA and methicillin susceptible staphylococci
- Bone infections due to susceptible isolates of MRSA and lower respiratory tract infections due to susceptible isolates of MRSA and methicillin susceptible staphylococci

1.9 Usage

To reduce the development of drug-resistant bacteria and maintain the effectiveness of Vancomycin Hydrochloride for Injection and other antibacterial drugs, Vancomycin Hydrochloride for Injection should be used only to treat or prevent infections that are proven or strongly suspected to be caused by susceptible bacteria. When culture and susceptibility information are available, they should be considered in selecting or modifying antibacterial therapy. In the absence of such data, local epidemiology and susceptibility patterns may contribute to the empiric selection of therapy.

2 DOSAGE AND ADMINISTRATION

2.1 Important Administration Instructions for Intravenous Use

- To reduce the risk of infusion related adverse reactions, administer diluted Vancomycin Hydrochloride for Injection by intravenous infusion over 60 minutes or greater [see Warnings and Precautions (5.5) and Adverse Reactions (6.1)].
- Diluted Vancomycin Hydrochloride for Injection concentrations of no more than 5 mg/mL are recommended in adults [see Dosage and Administration (2.2)]. See also age-specific recommendations [see Dosage and Administration (2.2, 2.3)]. In selected patients in need of fluid restriction, a concentration up to 10 mg/mL may be used. Infusion related events may occur, however, at any rate or concentration [see Warnings and Precautions (5.5)].
- Other drugs should not be added to the diluted Vancomycin Hydrochloride for Injection [see Dosage and Administration (2.7)].
- Administer diluted Vancomycin Hydrochloride for Injection prior to intravenous anesthetic agents to reduce the risk of infusion related adverse reactions [see Warnings and Precautions (5.5)].
- Administer diluted Vancomycin Hydrochloride for Injection by a secure intravenous route of administration to avoid local irritation and phlebitis reactions [see Warnings and Precautions (5.6)].

2.2 Intravenous Dosage in Adult and Pediatric Patients with Normal Renal Function

Dosage in Adult Patients

The usual daily intravenous dose is 2 grams (g) divided either as 500 mg every 6 hours or 1 g every 12 hours. Administer each dose by intravenous infusion over a period of 60 minutes or greater. Other patient factors, such as age or obesity, may call for modification of the usual intravenous daily dose.

Dosage in Pediatric Patients Aged 1 Month and Older

The usual intravenous dosage of vancomycin is 10 mg/kg per dose given every 6 hours. Each dose should be administered over a period of at least 60 minutes. Close monitoring of serum concentrations of vancomycin may be warranted in these patients.

Dosage in Pediatric Patients Younger than 1 Month of Age

In pediatric patients, up to the age of 1 month, the total daily intravenous dosage may be lower. In neonates, an initial dose of 15 mg/kg is suggested, followed by 10 mg/kg every 12 hours for pediatric patients in the 1st week of life and every 8 hours thereafter up to the age of 1 month. Each dose should be administered over 60 minutes. In premature infants, vancomycin clearance decreases as postconceptional age decreases. Therefore, longer dosing intervals may be necessary in premature infants. Close monitoring of serum concentrations of vancomycin is recommended in these patients.

2.3 Orally Administered Dosage in Adult and Pediatric Patients

Dosage in Adult Patients

- C. difficile-associated diarrhea: The recommended dose is 125 mg administered orally 4 times daily for 10 days.
- Staphylococcal enterocolitis: Total daily dosage is 500 mg to 2 g administered orally in 3 or 4 divided doses for 7 days to 10 days.

Dosage in Pediatric Patients (Less than 18 years of age)

For both C. difficile-associated diarrhea and staphylococcal enterocolitis, the usual daily dosage is 40 mg/kg in 3 or 4 divided doses for 7 days to 10 days. The total daily dosage should not exceed 2 g.

2.4 Intravenous Dosage in Patients with Renal Impairment

Dosage adjustment must be made in adult and pediatric patients with renal impairment. The initial dose should be no less than 15 mg/kg, in adult patients with any degree of renal impairment.

In premature infants and the elderly, greater dosage reductions than expected may be necessary because of decreased renal function. Measure trough vancomycin serum concentrations to guide therapy, especially in seriously ill patients with changing renal function.

For functionally anephric patients, an initial dose of 15 mg/kg of body weight should be given to achieve prompt therapeutic serum concentration. A dose of 1.9 mg/kg/24 hr should be given after the initial dose of 15 mg/kg.

2.5 Directions for the Preparation, Dilution, and Storage of the Single-Dose Vials for Intravenous Use

Preparation

Vancomycin Hydrochloride for Injection must be reconstituted and further diluted. No preservative is present in this product. Aseptic technique must be used in the preparation of final IV solution.

Reconstitution of the Spray-dried Powder:At the time of use, reconstitute the vials of Vancomycin Hydrochloride for Injection with Sterile Water for Injection to a concentration of 50 mg of vancomycin/mL (see following table for volume of diluent).

Vancomycin Strength per Vial | Volume of Diluent
500 mg | 10 mL
750 mg | 15 mL
1 g | 20 mL
1.25 g | 25 mL
1.5 g | 30 mL

After reconstitution, the vials may be stored at 2°C to 8°C (36°F to 46°F) for 96 hours without significant loss of potency.

Dilution

Reconstituted solutions of vancomycin (50 mg/mL) must be further diluted. A dose of 500 mg (10 mL) must be diluted with at least 100 mL of a suitable infusion solution. For doses of 750 mg (15 mL), at least 150 mL of solution must be used. For doses of 1 gram (20 mL), at least 200 mL of solution must be used. For doses of 1.25 gram (25 mL), at least 250 mL of solution must be used. For doses of 1.5 gram (30 mL), at least 300 mL of solution must be used. The desired dose diluted in this manner should be administered by intermittent IV infusion over a period of at least 60 minutes.

Parenteral drug products should be visually inspected for particulate matter and discoloration prior to administration, whenever solution and container permit.

2.6 Compatibility with Intravenous Fluids for Intravenous Use

The following diluents are physically and chemically compatible with approximately 4.5 mg/mL of vancomycin hydrochloride:

5% Dextrose Injection, USP

5% Dextrose Injection and 0.9% Sodium Chloride Injection, USP

Lactated Ringer’s Injection, USP

5% Dextrose and Lactated Ringer’s Injection, USP

0.9% Sodium Chloride Injection, USP

2.7 Incompatibilities for Intravenous Use

Vancomycin Hydrochloride for Injection reconstituted solution has a low pH and may cause chemical or physical instability when it is mixed with other compounds.

Mixtures of solutions of vancomycin and beta-lactam antibacterial drugs have been shown to be physically incompatible. The likelihood of precipitation increases with higher concentrations of vancomycin. It is recommended to adequately flush the intravenous lines between the administration of these antibacterial drugs. It is also recommended to dilute solutions of vancomycin to 5 mg/mL or less.

2.8 Preparation of Vancomycin Hydrochloride for Injection for Oral Administration

Preparation of the Single-Dose Vial for Oral Use

1. Reconstitute Vancomycin Hydrochloride for Injection to 100 mg/mL by adding the appropriate amount of sterile water for injection:
  Table 1: Reconstitution-Volume of Sterile Water for Injection to be Added
  Vancomycin Hydrochloride for Injection Strength per Vial | Volume of Sterile Water for Injection to be added to achieve 100 mg/mL Vancomycin Hydrochloride Solution
  500 mg | 5 mL
  750 mg | 7.5 mL
  1 g | 10 mL
  1.25 g | 12.5 mL
  1.5 g | 15 mL
2. Sweeteners may be added to the solution to improve the taste for oral administration following the steps outlined in Instructions for How to Prepare and Add Sweeteners below.

Instructions for How to Prepare and Add Sweeteners

1. Prepare the sweetening agent separately from the reconstituted Vancomycin hydrochloride solution in a plastic container following one of the preparation options below:

- Mix sucrose and sterile water for injection in a 1:2 ratio (e.g., 10 g sucrose and 20 mL sterile water for injection) OR
- Mix agave nectar with an equal volume of sterile water for injection

2. Mix the sweetening agent with the reconstituted Vancomycin hydrochloride solution in a 3:1 ratio (e.g., 30 mL sweetening agent with 10 mL vancomycin solution) to obtain a sweetened solution containing 25 mg/mL of vancomycin that is suitable for oral administration.

The diluted solution may be administered orally or via a nasogastric tube [see Dosage and Administration (2.3)].

2.9 Storage of Reconstituted and Diluted Vancomycin Hydrochloride for Injection for Intravenous or Oral Administration

Intravenous Administration:

Administer the compounded mixtures within 4 hours after preparation when storing at room temperature and 6 days when stored refrigerated (14 days for solutions made with 0.9% sodium chloride and 5% dextrose).

Oral Administration:

Store the diluted solution for oral use in a plastic container refrigerated at 2°C to 8°C (36°F to 46°F) for up to 10 days.

3 DOSAGE FORMS AND STRENGTHS

Vancomycin Hydrochloride for Injection is a sterile white, almost white to tan to brown, spray-dried powder in single-dose vials each containing vancomycin hydrochloride equivalent to 500 mg, 750 mg, 1 gram, 1.25 gram or 1.5 gram vancomycin base.

4 CONTRAINDICATIONS

Vancomycin Hydrochloride for Injection is contraindicated in patients with known hypersensitivity to vancomycin and polysorbate 80.

5 WARNINGS AND PRECAUTIONS

5.1 Nephrotoxicity

Vancomycin Hydrochloride for Injection administered intravenously or orally can result in acute kidney injury (AKI), including acute renal failure, mainly due to interstitial nephritis or less commonly acute tubular necrosis. AKI is manifested by increasing blood urea nitrogen (BUN) and serum creatinine (Cr). The risk of AKI increases with higher vancomycin serum levels, prolonged exposure, concomitant administration of other nephrotoxic drugs, concomitant administration of piperacillin-tazobactam [see Drug Interactions (7.2)], volume depletion, pre-existing renal impairment and in critically ill patients and patients with co-morbid conditions that predispose to renal impairment.

Monitor serum vancomycin concentrations and renal function in all patients receiving Vancomycin Hydrochloride for Injection intravenously.

Nephrotoxicity (e.g., reports of renal failure, renal impairment, blood creatine increased) has occurred following oral vancomycin hydrochloride capsule therapy in randomized controlled clinical studies and can occur either during or after completion of therapy. The risk of nephrotoxicity is increased in patients >65 years of age [see Adverse Reactions (6.1) and Use in Specific Populations (8.5)]. In patients over 65 years of age, including those with normal renal function prior to treatment, renal function should be monitored during and following treatment with oral Vancomycin Hydrochloride for Injection therapy to detect potential vancomycin induced nephrotoxicity.

More frequent monitoring is recommended in patients with comorbidities that predispose to impairment in renal function or are concomitantly receiving other nephrotoxic drugs, in critically ill patients, in patients with changing renal function, and in patients requiring higher therapeutic vancomycin levels. If acute kidney injury occurs, discontinue Vancomycin Hydrochloride for Injection or reduce the dose.

5.2 Ototoxicity

Ototoxicity has occurred in patients administered vancomycin intravenously or orally. It may be transient or permanent. Ototoxicity manifests as tinnitus, hearing loss, dizziness or vertigo. The risk is higher in older patients, patients who are receiving higher doses, who have an underlying hearing loss, who are receiving concomitant therapy with another ototoxic agent, such as an aminoglycoside or who have underlying renal impairment. Monitor for signs and symptoms of ototoxicity during oral or intravenous therapy with Vancomycin Hydrochloride for Injection. Discontinue Vancomycin Hydrochloride for Injection if ototoxicity occurs. Serial tests of auditory function may be helpful in order to minimize the risk of ototoxicity.

5.3 Severe Dermatologic Reactions

Severe dermatologic reactions such as toxic epidermal necrolysis (TEN), Stevens-Johnson syndrome (SJS), drug reaction with eosinophilia and systemic symptoms (DRESS), acute generalized exanthematous pustulosis (AGEP), and linear IgA bullous dermatosis (LABD) have been reported in association with the use of vancomycin. Cutaneous signs or symptoms reported include skin rashes, mucosal lesions, and blisters.

Discontinue Vancomycin Hydrochloride for Injection at the first appearance of signs and symptoms of TEN, SJS, DRESS, AGEP, or LABD.

5.4 Neutropenia

Reversible neutropenia has been reported in patients administered vancomycin intravenously or orally. Patients who will undergo prolonged therapy with Vancomycin Hydrochloride for Injection or those who are receiving concomitant drugs which may cause neutropenia should have periodic monitoring of the leukocyte count.

5.5 Infusion Reactions

Hypotension, including shock and cardiac arrest, wheezing, dyspnea, urticaria, muscular and chest pain may occur with rapid Vancomycin Hydrochloride for Injection intravenous administration. The reactions may be more severe in younger patients, particularly children, and in patients receiving concomitant muscle relaxant anesthetics. Rapid intravenous administration of Vancomycin Hydrochloride for Injection may also be associated with vancomycin infusion reaction, which manifests as pruritus and erythema that involves the face, neck and upper torso. Infusion-related adverse reactions are related to both the concentration and the rate of administration of Vancomycin Hydrochloride for Injection. Infusion-related adverse reactions may occur, however, at any rate or concentration.

Administer Vancomycin Hydrochloride for Injection in a diluted solution over a period of 60 minutes or greater to reduce the risk of infusion-related adverse reactions. In selected patients in need of fluid restriction, a concentration up to 10 mg/mL may be used; use of such higher concentrations may increase the risk of infusion-related adverse reactions [see Nonclinical Toxicology (13.2)]. Administer prior to intravenous anesthetic agents when feasible. Stop the infusion if a reaction occurs.

5.6 Phlebitis and Adverse Reactions with Unapproved Routes of Administration

Inflammation at the site of injection of vancomycin has been reported. Vancomycin is irritating to tissue and must be given by a secure intravenous route of administration to reduce the risk of local irritation and phlebitis. Thrombophlebitis may occur, the frequency and severity of which can be minimized by slow infusion of the drug and by rotation of venous access sites.

Administration of Vancomycin Hydrochloride for Injection by intramuscular (IM), intraperitoneal, intrathecal intraventricular, or intravitreal routes has not been approved and is not recommended. The safety and efficacy of vancomycin administered by these routes of administration have not been established by adequate and well controlled trials. Pain, tenderness, and necrosis occur with IM injection of vancomycin or with inadvertent extravasation. Intraperitoneal administration during continuous ambulatory peritoneal dialysis (CAPD) can result in chemical peritonitis. Manifestations range from cloudy dialysate alone to a cloudy dialysate accompanied by variable degrees of abdominal pain and fever. This syndrome appears to be resolved after discontinuation of intraperitoneal vancomycin.

About 60% of an intraperitoneal dose of vancomycin administered during peritoneal dialysis is absorbed systemically in 6 hours. Serum concentrations of about 10 mcg/mL are achieved by intraperitoneal injection of 30 mg/kg of vancomycin. However, the safety and efficacy of the intraperitoneal use of vancomycin has not been established in adequate and well-controlled trials.

5.7 Clostridioides difficile-Associated Diarrhea (CDAD)

Clostridioides difficile-associated diarrhea (CDAD) has been reported with use of nearly all antibacterial agents, including with intravenous administration of vancomycin and may range in severity from mild diarrhea to fatal colitis. Treatment with antibacterial agents alters the normal flora of the colon leading to overgrowth of C. difficile.

C. difficile produces toxins A and B which contribute to the development of CDAD. Hypertoxin producing strains of C. difficile cause increased morbidity and mortality, as these infections can be refractory to antimicrobial therapy and may require colectomy. CDAD must be considered in all patients who present with diarrhea following antibacterial use. Careful medical history is necessary since CDAD has been reported to occur over two months after the administration of antibacterial agents. If CDAD is suspected or confirmed, ongoing antibacterial use not directed against C. difficile may need to be discontinued. Appropriate fluid and electrolyte management, protein supplementation, antibacterial treatment of C. difficile, and surgical evaluation should be instituted as clinically indicated.

Clinically significant serum concentrations of vancomycin have been reported in some patients being treated for active C. difficile-induced pseudomembranous colitis after multiple oral doses of vancomycin [see Warnings and Precautions (5.10)].

Prolonged use of Vancomycin Hydrochloride for Injection may result in the overgrowth of non-susceptible microorganisms. Careful observation of the patient is essential. If superinfection occurs during therapy, appropriate measures should be taken. There have been reports of pseudomembranous colitis due to C. difficile developing in patients who received intravenous vancomycin.

5.8 Hemorrhagic Occlusive Retinal Vasculitis (HORV)

Hemorrhagic occlusive retinal vasculitis, including permanent loss of vision, occurred in patients receiving intracameral or intravitreal administration of vancomycin during or after cataract surgery. The safety and efficacy of vancomycin administered by the intracameral or the intravitreal route have not been established by adequate and well-controlled trials. Vancomycin Hydrochloride for Injection (intravenously and orally administered) is not indicated for the prophylaxis of endophthalmitis.

5.9 Development of Drug-Resistant Bacteria

Prescribing Vancomycin Hydrochloride for Injection (intravenously and orally administered) in the absence of a proven or strongly suspected bacterial infection or a prophylactic indication is unlikely to provide benefit to the patient and increases the risk of the development of drug-resistant bacteria.

5.10 Potential for Systemic Absorption after Oral Administration

Clinically significant serum concentrations have been reported in some patients who have taken multiple oral doses of oral vancomycin for active C. difficile-associated diarrhea. Some patients with inflammatory disorders of the intestinal mucosa also may have significant systemic absorption of vancomycin. These patients may be at risk for the development of adverse reactions associated with higher doses of oral vancomycin; therefore, monitoring of serum concentrations of vancomycin may be appropriate in some instances, e.g., in patients with renal insufficiency and/or colitis or in those receiving concomitant therapy with an aminoglycoside antibacterial drug.

6 ADVERSE REACTIONS

The following clinically significant adverse reactions are described elsewhere in the labeling:

- Nephrotoxicity [see Warnings and Precautions (5.1)]
- Ototoxicity [see Warnings and Precautions (5.2)]
- Severe Dermatologic Reactions [see Warnings and Precautions (5.3)]
- Neutropenia [see Warnings and Precautions (5.4)]
- Infusion Reactions [see Warnings and Precautions (5.5)]
- Clostridioides difficile-Associated Diarrhea [see Warnings and Precautions (5.7)]

6.1 Clinical Trials Experience

Because clinical trials are conducted under widely varying conditions, adverse reaction rates observed in the clinical trials of a drug cannot be directly compared to rates in the clinical trials of another drug and may not reflect the rates observed in practice.

Adverse Reactions in Patients Receiving Intravenously and Orally Administered Vancomycin

The following adverse reactions associated with the use of intravenously and orally administered vancomycin were identified in clinical trials:

Renal and urinary disorders: Acute kidney injury and interstitial nephritis [see Warnings and Precautions (5.1)]

Ear and labyrinth disorders: Tinnitus, hearing loss, vertigo [see Warnings and Precautions (5.2)]

Skin and subcutaneous tissue disorders: Erythema (especially of the face, neck and upper torso) and pruritus which are manifestations of rashes including exfoliative dermatitis, toxic epidermal necrolysis (TEN), Stevens-Johnson syndrome (SJS), Linear IgA bullous dermatosis (LABD) [see Warnings and Precautions (5.3)].

Blood and lymphatic system disorders: Agranulocytosis, neutropenia, pancytopenia, leukopenia, thrombocytopenia, eosinophilia [see Warnings and Precautions (5.4)]

Immune system disorders: Hypersensitivity reactions including anaphylaxis and vancomycin infusion reaction [see Warnings and Precautions (5.5)]

General disorders and administration site conditions: General discomfort, fever, chills, phlebitis, injection site irritation, injection site pain and necrosis following intramuscular injection, chemical peritonitis following intraperitoneal administration. Vancomycin Hydrochloride for Injection is not approved for intramuscular and intraperitoneal administration [see Warnings and Precautions (5.6)]

Gastrointestinal disorders: Pseudomembranous colitis [see Warnings and Precautions (5.7)]

Cardiac disorders: Cardiac arrest, chest pain

Laboratory abnormalities: Elevated blood urea nitrogen, elevated serum creatinine

Musculoskeletal and connective tissue disorders: Muscle pain

Nervous system disorders: Dizziness

Respiratory, thoracic and mediastinal disorders: Wheezing, dyspnea

Vascular disorders: Hypotension, shock, vasculitis

Adverse Reactions in Patients Receiving Oral Administration of Vancomycin Hydrochloride Capsules

The data described below reflect exposure to vancomycin hydrochloride capsules in 260 adult subjects in two Phase 3 clinical trials for the treatment of diarrhea associated with C. difficile. In both trials, subjects received vancomycin hydrochloride capsules 125 mg orally four times daily. The mean duration of treatment was 9.4 days. The median age of patients was 67, ranging between 19 and 96 years of age. Patients were predominantly Caucasian (93%) and 52% were male.

Adverse reactions occurring in ≥5% of vancomycin hydrochloride capsules-treated subjects are shown in Table 2. The most common adverse reactions associated with vancomycin hydrochloride capsules (≥10%) were nausea, abdominal pain, and hypokalemia.

Table 2: Common (≥5%) Adverse Reactionsa for Vancomycin Hydrochloride Capsules Reported in Clinical Trials for Treatment of Diarrhea Associated with C. difficile

System/Organ Class | Adverse Reaction | Vancomycin Hydrochloride Capsule % (N=260)
Gastrointestinal disorders | Nausea Abdominal pain Vomiting Diarrhea Flatulence | 17 15 9 9 8
General disorders and administration site conditions | Pyrexia Edema peripheral Fatigue | 9 6 5
Infections and infestations | Urinary tract infection | 8
Metabolism and nutrition disorders | Hypokalemia | 13
Musculoskeletal and connective tissue disorders | Back pain | 6
Nervous system disorders | Headache | 7
aAdverse reaction rates were derived from the incidence of treatment-emergent adverse events.

Nephrotoxicity (e.g., reports of renal failure, renal impairment, blood creatinine increased) occurred in 5% of subjects treated with vancomycin hydrochloride capsules. Nephrotoxicity following vancomycin hydrochloride capsules typically first occurred within one week after completion of treatment (median day of onset was Day 16). Nephrotoxicity following vancomycin hydrochloride capsules occurred in 6% of subjects >65 years of age and 3% of subjects ≤65 years of age.

The incidences of hypokalemia, urinary tract infection, peripheral edema, insomnia, constipation, anemia, depression, vomiting, and hypotension were higher among subjects >65 years of age than in subjects ≤65 years of age.

Discontinuation of study drug due to adverse events occurred in 7% of subjects treated with vancomycin hydrochloride capsules. The most common adverse events leading to discontinuation of vancomycin hydrochloride capsules were C. difficile colitis (<1%), nausea (<1%), and vomiting (<1%).

6.2 Postmarketing Experience

The following adverse reactions have been identified during postmarketing use of vancomycin (administered orally and intravenously). Because these reactions are reported voluntarily from a population of uncertain size, it is not possible to reliably estimate their frequency or establish a causal relationship to drug exposure.

Skin and Subcutaneous Tissue Disorders: Drug reaction with eosinophilia and systemic symptoms (DRESS), acute generalized exanthematous pustulosis (AGEP) [see Warnings and Precautions (5.3)].

Ototoxicity: Cases of hearing loss associated with intravenously administered vancomycin have been reported. Most of these patients had kidney dysfunction or a preexisting hearing loss or were receiving concomitant treatment with an ototoxic drug [see Warnings and Precautions (5.2)]. Vertigo, dizziness, and tinnitus have been reported.

Hematopoietic: Reversible neutropenia, usually starting 1 week or more after onset of intravenous therapy with vancomycin or after a total dose of more than 25 g, has been reported for several dozen patients. Neutropenia appears to be promptly reversible when vancomycin is discontinued. Thrombocytopenia has been reported.
Miscellaneous: Patients have been reported to have had anaphylaxis, drug fever, chills, nausea, eosinophilia, and cases of vasculitis in association with the administration of vancomycin.

A condition has been reported with oral vancomycin that is similar to the intravenous vancomycin-induced syndrome with symptoms consistent with anaphylactoid reactions, including hypotension, wheezing, dyspnea, urticaria, pruritus, flushing of the upper body (“vancomycin infusion reaction”), pain and muscle spasm of the chest and back [see Warnings and Precautions (5.5)]. These reactions usually resolve within 20 minutes but may persist for several hours.

7 DRUG INTERACTIONS

7.1 Anesthetic Agents

Concomitant administration of vancomycin and anesthetic agents has been associated with erythema and histamine-like flushing [see Warnings and Precautions (5.5) and Use in Specific Populations (8.4)].

7.2 Piperacillin-Tazobactam

Studies have detected an increased incidence of acute kidney injury in patients administered concomitant piperacillin/tazobactam and vancomycin as compared to vancomycin alone. Monitor kidney function in patients receiving concomitant piperacillin/tazobactam and Vancomycin Hydrochloride for Injection. No pharmacokinetic interactions have been noted between piperacillin/tazobactam and vancomycin.

7.3 Ototoxic and/or Nephrotoxic Drugs

Concurrent and/or sequential systemic or topical use of other potentially, neurotoxic and/or nephrotoxic drugs requires more frequent monitoring of renal function.

8 USE IN SPECIFIC POPULATIONS

8.1 Pregnancy

Risk Summary

There are no available data on vancomycin use in pregnant women to inform a drug associated risk of major birth defects or miscarriage. Available published data on vancomycin use in pregnancy during the second and third trimesters have not shown an association with adverse pregnancy related outcomes (see Data). Vancomycin did not show adverse developmental effects when administered intravenously to pregnant rats and rabbits during organogenesis at doses less than or equal to the recommended maximum human dose (see Data). Systemic absorption of vancomycin is low following oral administration of vancomycin hydrochloride capsules; however, absorption may vary depending on various factors [see Clinical Pharmacology (12.3)].

The estimated background risk of major birth defects and miscarriage for the indicated population(s) is unknown. All pregnancies have a background risk of birth defect, loss, or other adverse outcomes. In the U.S. general population, the estimated background risk of major birth defects and miscarriage in clinically recognized pregnancies is 2% to 4% and 15% to 20%, respectively.

Data

Human Data

A published study evaluated hearing loss and nephrotoxicity in infants of 10 pregnant intravenous drug users treated with intravenously administered vancomycin for suspected or documented methicillin-resistant Staphylococcus-aureus (MRSA) infections in the second or third trimester. The comparison groups were 10 non-intravenous drug-dependent patients who received no treatment, and 10 untreated intravenous drug-dependent patients who served as substance abuse controls. No infant in the vancomycin exposed group had abnormal sensorineural hearing at 3 months of age or nephrotoxicity.
A published prospective study assessed outcomes in 55 pregnant women with a positive Group B streptococcus (GBS) culture and a high-risk penicillin allergy with resistance to clindamycin or unknown sensitivity who were administered vancomycin intravenously at the time of delivery. Vancomycin dosing ranged from the standard 1 g intravenously every 12 hours to 20 mg/kg intravenous every 8 hours (maximum individual dose 2 g). No major adverse reactions were recorded either in the mothers or their newborns. None of the newborns had sensorineural hearing loss. Neonatal renal function was not examined, but all of the newborns were discharged in good condition.

Animal Data

Vancomycin did not cause fetal malformations when administered during organogenesis to pregnant rats (gestation days 6 to 15) and rabbits (gestation days 6 to 18) at the equivalent recommended maximum human dose (based on body surface area comparisons) of 200 mg/kg/day IV to rats or 120 mg/kg/day IV to rabbits^1. No effects on fetal weight or development were seen in rats at the highest dose tested or in rabbits given 80 mg/kg/day (approximately 1 and 0.8 times the recommended maximum human dose based on body surface area, respectively). Maternal toxicity was observed in rats (at doses 120 mg/kg and above) and rabbits (at 80 mg/kg and above). There were no oral embryo-fetal toxicity studies conducted in animals with this Vancomycin Injection product.

8.2 Lactation

Risk Summary

Vancomycin is present in human milk following intravenous administration, however, there are insufficient data to inform the levels. There are no available data on vancomycin presence in milk following oral administration. Systemic absorption of vancomycin is low following oral administration of vancomycin hydrochloride capsules; however, absorption may vary depending on various factors [see Clinical Pharmacology (12.3)]. There are no data on the effects of vancomycin on the breastfed infant or milk production. The developmental and health benefits of breastfeeding should be considered along with the mother’s clinical need for Vancomycin Hydrochloride for Injection and any potential adverse effects on the breastfed infant from Vancomycin Hydrochloride for Injection or from the underlying maternal condition.

8.4 Pediatric Use

Vancomycin Hydrochloride for Injection administered intravenously is indicated in pediatric patients less than 18 years of age for the treatment of septicemia, infective endocarditis, skin and skin structure infections, bone infections and lower respiratory tract infections [see Indications and Usage (1.1 to 1.5) and Dosage and Administration (2.2)].

Vancomycin Hydrochloride for Injection administered orally is indicated in pediatric patients less than 18 years of age for the treatment of Clostridioides difficile-associated diarrhea and enterocolitis caused by Staphylococcus aureus (including methicillin-resistant strains) [see Indications and Usage (1.6, 1.7) and Dosage and Administration (2.3)].

In pediatric patients, monitor vancomycin serum concentration and renal function when administering Vancomycin Hydrochloride for Injection intravenously [see Dosage and Administration (2.2) and Warnings and Precautions (5.1)]. More severe infusion related reactions related to Vancomycin Hydrochloride for Injection administration may occur in pediatric patients. Concomitant administration of vancomycin and intravenous anesthetic agents has been associated with erythema and histamine-like flushing in all patients including pediatric patients [see Warnings and Precautions (5.5)].

8.5 Geriatric Use

Clinical studies with another vancomycin hydrochloride drug product in C. difficile-associated diarrhea have demonstrated that geriatric subjects are at increased risk of developing nephrotoxicity following treatment with oral vancomycin hydrochloride, which may occur during or after completion of therapy. In patients over 65 years of age, including those with normal renal function prior to treatment, renal function should be monitored during and following treatment with Vancomycin Hydrochloride for Injection to detect potential vancomycin induced nephrotoxicity [see Warnings and Precautions (5.1)] and Adverse Reactions (6.1)].

Patients over 65 years of age may take longer to respond to therapy compared to patients 65 years of age and younger. Clinicians should be aware of the importance of appropriate duration of Vancomycin Hydrochloride for Injection treatment in patients over 65 years of age and not discontinue or switch to alternative treatment prematurely.

Vancomycin Hydrochloride for Injection is known to be substantially excreted by the kidney, and the risk of adverse reactions to this drug may be greater in patients with impaired renal function. Because elderly patients are more likely to have decreased renal function, care should be taken in dose selection [see Dosage and Administration (2.4)], and it may be useful to monitor renal function [see Warnings and Precautions (5.1)].

8.6 Renal Impairment

Dosage adjustment must be made in patients with impaired renal function [see Dosage and Administration (2.3)]. Measure trough vancomycin serum concentrations to guide intravenous therapy, especially in seriously ill patients with changing renal function.

10 OVERDOSAGE

Supportive care is advised, with maintenance of glomerular filtration. Vancomycin is poorly removed by dialysis. Hemofiltration and hemoperfusion with polysulfone resin have been reported to result in increased vancomycin clearance.

For current information on the management of overdosage, contact the National Poison Control Center at 1-800-222-1222 or www.poison.org.

11 DESCRIPTION

Vancomycin Hydrochloride for Injection contains the hydrochloride salt of vancomycin, a tricyclic glycopeptide antibacterial derived from Amycolatopsis orientalis (formerly Nocardia orientalis). The chemical name for vancomycin hydrochloride is (Sa)-(3S,6R,7R,22R,23S,26S,36R,38aR)-44-[[2-O-(3-Amino-2,3,6-trideoxy-3-C-methyl-α-L-lyxo-hexopyranosyl)-β-D-glucopyranosyl]oxy]-3-(carbamoylmethyl)-10,19-dichloro-2,3,4,5,6,7,23,24,25,26,36,37,38,38a-tetradecahydro-7,22,28,30,32-pentahydroxy-6-[(2R)-4-methyl-2-(methylamino)valeramido]-2,5,24,38,39-pentaoxo-22H-8,11:18,21-dietheno-23,36-(iminomethano)-13,16:31,35-dimetheno-1H,16H-[l,6,9]oxadiazacyclohexadecino[4,5-m][10,2,16]-benzoxadiazacyclotetracosine-26-carboxylic acid, monohydrochloride. The molecular formula is C66H75Cl2N9O24 • HCl and the molecular weight is 1,485.71. Vancomycin hydrochloride has the following structural formula:

Vancomycin Hydrochloride for Injection is a sterile, preservative-free, white, almost white to tan to brown, spray-dried powder, for preparing intravenous (IV) infusions, in single-dose vials each containing the equivalent of 500 mg, 750 mg, 1 g, 1.25 g or 1.5 g vancomycin base. Each 500 mg vial contains 500 mg vancomycin (equivalent to 513 mg vancomycin hydrochloride), 125 mg trehalose, 0.05 mg polysorbate 80, and hydrochloric acid used to adjust the pH. Each 750 mg vial contains 750 mg vancomycin (equivalent to 769 mg vancomycin hydrochloride), 187.5 mg trehalose, 0.075 mg polysorbate 80, and hydrochloric acid used to adjust the pH. Each 1 g vial contains 1 g vancomycin (equivalent to 1.025 g vancomycin hydrochloride), 250 mg trehalose, 0.1 mg polysorbate 80, and hydrochloric acid used to adjust the pH. Each 1.25 g vial contains 1.25 g vancomycin (equivalent to 1.28 g vancomycin hydrochloride), 312.5 mg trehalose, 0.125 mg polysorbate 80, and hydrochloric acid used to adjust the pH. Each 1.5 g vial contains 1.5 g vancomycin (equivalent to 1.54 g vancomycin hydrochloride), 375 mg trehalose, 0.15 mg polysorbate 80, and hydrochloric acid used to adjust the pH.

The spray-dried powder is reconstituted with Sterile Water for Injection which forms a clear solution and subsequently diluted prior to intravenous or oral administration [see Dosage and Administration (2.5, 2.8)]. Vancomycin Hydrochloride for Injection may also be diluted with a sweetening agent for oral administration [see Dosage and Administration (2.8)].

12 CLINICAL PHARMACOLOGY

12.1 Mechanism of Action

Vancomycin is an antibacterial drug [see Microbiology (12.4)].

12.2 Pharmacodynamics

The pharmacodynamics of vancomycin is unknown.

12.3 Pharmacokinetics

General Pharmacokinetics

In subjects with normal kidney function, multiple intravenous dosing of 1 g of vancomycin (15 mg/kg) infused over 60 minutes produces mean plasma concentrations of approximately 63 mcg/mL immediately after the completion of infusion, mean plasma concentrations of approximately 23 mcg/mL 2 hours after infusion, and mean plasma concentrations of approximately 8 mcg/mL 11 hours after the end of the infusion. Multiple dosing of 500 mg infused over 30 minutes produces mean plasma concentrations of about 49 mcg/mL at the completion of infusion, mean plasma concentrations of about 19 mcg/mL 2 hours after infusion, and mean plasma concentrations of about 10 mcg/mL 6 hours after infusion. The plasma concentrations during multiple dosing are like those after a single dose.

Absorption

Vancomycin is poorly absorbed after oral administration. During multiple dosing of 250 mg every 8 hours for 7 doses, fecal concentrations of vancomycin in volunteers exceeded 100 mg/kg in the majority of samples. No blood concentrations were detected, and urinary recovery did not exceed 0.76%. In anephric subjects with no inflammatory bowel disease who received vancomycin oral solution 2 g for 16 days, blood concentrations of vancomycin were less than or equal to 0.66 mcg/mL in 2 of 5 subjects. No measurable blood concentrations were attained in the other 3 subjects. Following doses of 2 g daily, concentrations of drug were >3100 mg/kg in the feces and <1 mcg/mL in the serum of subjects with normal renal function who had C. difficile-associated diarrhea. After multiple-dose oral administration of vancomycin, measurable serum concentrations may occur in patients with active C. diffifile-associated diarrhea, and, in the presence of renal impairment, the possibility of accumulation exists. It should be noted that the total systemic and renal clearances of vancomycin are reduced in the elderly [see Use in Specific Populations (8.5)].

Distribution

The volume of distribution ranges from 0.3 to 0.43 L/kg after intravenous administration. Vancomycin is approximately 55% serum protein bound as measured by ultrafiltration at vancomycin serum concentrations of 10 to 100 mcg/mL. After intravenous administration of vancomycin, inhibitory concentrations are present in pleural, pericardial, ascitic, and synovial fluids; in urine; in peritoneal dialysis fluid; and in atrial appendage tissue. Vancomycin does not readily diffuse across normal meninges into the spinal fluid; but, when the meninges are inflamed, penetration into the spinal fluid occurs.

Elimination

Mean plasma clearance is about 0.058 L/kg/h, and mean renal clearance is about 0.048 L/kg/h.
The mean elimination half-life of vancomycin from plasma is 4 to 6 hours in subjects with normal renal function. In anephric patients, the mean elimination half-life is 7.5 days. Total body and renal clearance of vancomycin may be reduced in the elderly.

Metabolism

There is no apparent metabolism of vancomycin.

Excretion

In the first 24 hours after intravenous administration, about 75% of an administered dose of vancomycin is excreted in urine by glomerular filtration. Renal impairment slows excretion of vancomycin.

12.4 Microbiology

Mechanism of Action

The bactericidal action of vancomycin results primarily from inhibition of cell-wall biosynthesis. In addition, vancomycin alters bacterial-cell-membrane permeability and RNA synthesis.

Resistance

Vancomycin is not active in vitro against gram-negative bacilli, mycobacteria, or fungi. There is no cross-resistance between vancomycin and other antibacterials.

C. difficile

Isolates of C. difficile generally have vancomycin minimal inhibitory concentrations (MICs) of <1 mcg/mL; however, vancomycin MICs ranging from 4 mcg/mL to 16 mcg/mL have been reported. The mechanism which mediates C. difficile’s decreased susceptibility to vancomycin has not been fully elucidated.

S. aureus

S. aureus isolates with vancomycin MICs as high as 1024 mcg/mL have been reported. The exact mechanism of this resistance is not clear but is believed to be due to cell wall thickening and potentially the transfer of genetic material.

Interaction with Other Antimicrobials

The combination of vancomycin and an aminoglycoside acts synergistically in vitro against many isolates of Staphylococcus aureus, Streptococcus gallolyticus (previously known as Streptococcus bovis), Enterococcus species, and the viridans group streptococci.

Antimicrobial Activity

Vancomycin has been shown to be active against most isolates of the following microorganisms, both in vitro and in clinical infections [see Indications and Usage (1)].

Aerobic bacteria

Gram-positive bacteria

Corynebacterium species
Enterococcus species (including Enterococcus faecalis)
Staphylococcus aureus (including methicillin-resistant and methicillin-susceptible isolates)
Coagulase negative staphylococci (including S. epidermidis and methicillin-resistant isolates)
Streptococcus gallolyticus (previously known as Streptococcus bovis)
Viridans group streptococci

Anaerobic bacteria

Gram-positive bacteria

Clostridioides difficile isolates associated with C. difficile associated diarrhea.

The following in vitro data are available, but their clinical significance is unknown. At least 90 percent of the following bacteria exhibit an in vitro minimum inhibitory concentration (MIC) less than or equal to the susceptible breakpoint for vancomycin against isolates of similar genus or organism group. However, the efficacy of vancomycin in treating clinical infections caused by these bacteria has not been established in adequate and well-controlled clinical trials.

Aerobic bacteria

Gram-positive bacteria

Listeria monocytogenes

Streptococcus pyogenes

Streptococcus pneumoniae

Streptococcus agalactiae

Anaerobic bacteria

Gram-positive bacteria

Actinomyces species

Lactobacillus species

Susceptibility Testing

For specific information regarding susceptibility test interpretive criteria and associated test methods and quality control standards recognized by FDA for this drug, please see: https://www.fda.gov/STIC.

13 NONCLINICAL TOXICOLOGY

13.1 Carcinogenesis, Mutagenesis, Impairment of Fertility

No long-term carcinogenesis studies in animals have been conducted.

At concentrations up to 1000 mcg/mL, vancomycin had no mutagenic effect in vitro in the mouse lymphoma forward mutation assay or the primary rat hepatocyte unscheduled DNA synthesis assay. The concentrations tested in vitro were above the peak plasma vancomycin concentrations of 20 to 40 mcg/mL usually achieved in humans after slow infusion of the maximum recommended dose of 1 g. Vancomycin had no mutagenic effect in vivo in the Chinese hamster sister chromatid exchange assay (400 mg/kg IP) or the mouse micronucleus assay (800 mg/kg IP).

No definitive fertility studies have been conducted.

13.2 Animal Toxicology and/or Pharmacology

In animal studies, hypotension and bradycardia occurred in dogs receiving an intravenous infusion of vancomycin hydrochloride 25 mg/kg, at a concentration and infusion rate higher than recommended (concentration of 25 mg/mL and an infusion rate of 13.3 mL/min).

In a 4-week repeat-dose toxicokinetic study, electrocardiograms were obtained from dogs receiving Vancomycin Hydrochloride for Injection by the IV route, twice daily at 33 mg/kg (at a concentration of 10 mg/mL, over 30 minutes), for a total daily vancomycin dose of 66 mg/kg/day. No bradycardia was observed in the dogs when the pretest heart rates were compared to the heart rates observed 1 to 2 hours after the first daily dose during week 4.

15 REFERENCES

1. Byrd RA., Gries CL, Buening M.: Developmental Toxicology Studies of Vancomycin Hydrochloride Administered Intravenously to Rats and Rabbits. Fundam Appl Toxicol 1994; 23: 590-597.

16 HOW SUPPLIED/STORAGE AND HANDLING

How supplied

Vancomycin Hydrochloride for Injection is a white, almost white to tan to brown, sterile spray-dried powder in single-dose vials each containing vancomycin hydrochloride equivalent to 500 mg, 750 mg, 1 g, 1.25 g or 1.5 g of vancomycin base. The vial stopper is not made with natural rubber latex.

NDC No.; Unit of sale | Strength; Unit of Sale | NDC for Each; Vial
0143-9161-10; Unit of 10 | Vancomycin Hydrochloride for Injection, equivalent to 500 mg vancomycin in a flip-top vial, in packages of 10 vials. | 0143-9161-01
0143-9161-25; Unit of 25 | Vancomycin Hydrochloride for Injection, equivalent to 500 mg vancomycin in a flip-top vial, in packages of 25 vials. | 0143-9161-01
0143-9473-10 Unit of 10 | Vancomycin Hydrochloride for Injection, equivalent to 750 mg vancomycin in a flip-top vial, in packages of 10 vials. | 0143-9473-01
0143-9162-10 Unit of 10 | Vancomycin Hydrochloride for Injection, equivalent to 1 g vancomycin in a flip-top vial in packages of 10 vials. | 0143-9162-01
0143-9474-10 Unit of 10 | Vancomycin Hydrochloride for Injection, equivalent to 1.25 g vancomycin in a flip-top vial in packages of 10 vials. | 0143-9474-01
0143-9475-10 Unit of 10 | Vancomycin Hydrochloride for Injection, equivalent to 1.5 g vancomycin in a flip-top vial in packages of 10 vials. | 0143-9475-01

Storage

Store at 20°C to 25°C (68°F to 77°F). Brief exposure to 15°C to 30°C (59°F to 86°F) is permitted [See USP Controlled Room Temperature]. Storage after reconstitution and dilution is described elsewhere in the labeling [see Dosage and Administration (2.5, 2.8)].

17 PATIENT COUNSELING INFORMATION

Acute Kidney Injury

Advise patients that Vancomycin Hydrochloride for Injection can result in kidney damage and that blood tests are required to monitor vancomycin blood levels and kidney function during therapy [see Warnings and Precautions (5.1)].

Hearing Loss or Balance Problems

Advise patients that Vancomycin Hydrochloride for Injection may result in decreased hearing and to report hearing loss or balance problems to their health care provider [see Warnings and Precautions (5.2)].

Severe Dermatologic Reactions

Advise patients about the signs and symptoms of serious skin manifestations. Instruct patients to stop Vancomycin Hydrochloride for Injection immediately and promptly seek medical attention at the first signs or symptoms of skin rash, mucosal lesions or blisters [see Warnings and Precautions (5.3)].

Infusion Reactions During or After Intravenous Use

Advise patients that generalized skin redness, skin rash, itching, flushing, muscle pain, chest pain, shortness of breath, wheezing, or dizziness may occur during Vancomycin Hydrochloride for Injection infusion [see Warnings and Precautions (5.5)].

Diarrhea

Diarrhea is a common problem caused by antibacterial drugs, including vancomycin, which usually ends when the antibacterial drug is discontinued. Sometimes after starting treatment with antibacterial drugs, patients can develop watery and bloody stools (with or without stomach cramps and fever) even as late as two or more months after having taken the last dose of the antibacterial drug. If this occurs during treatment with Vancomycin Hydrochloride for Injection, patients should contact their physician as soon as possible [see Warnings and Precautions (5.7)].

Antibacterial Resistance

Patients should be counseled that antibacterial drugs including Vancomycin Hydrochloride for Injection should only be used to treat bacterial infections. They do not treat viral infections (e.g., the common cold). When Vancomycin Hydrochloride for Injection is prescribed to treat a bacterial infection, patients should be told that although it is common to feel better early in the course of therapy, the medication should be taken exactly as directed. Skipping doses or not completing the full course of therapy may (1) decrease the effectiveness of the immediate treatment and (2) increase the likelihood that bacteria will develop resistance and will not be treatable by Vancomycin Hydrochloride for Injection or other antibacterial drugs in the future.

Manufactured by:
Zhejiang Novus Pharmaceuticals Co., Ltd.
No. 125, Yuezhong Rd, Lihai Subdistrict,
Yuecheng District, Shaoxing, 312366, Zhejiang,
China

Distributed by:

Hikma Pharmaceuticals USA Inc.

Berkeley Heights, NJ 07922

Package Label - NDC 0143-9161-10 - NDC 0143-9161-01

Carton Label

NDC 0143-9161-10

Rx Only

Vancomycin Hydrochloride

for Injection

Equivalent to

500 mg*/ vial

Vancomycin

10 Vials

For Oral Use, see prescribing information.

For Intravenous Use

After Reconstitution Must Be Further Diluted Before Use

READ INSERT FOR PRECAUTIONS AND DIRECTIONS BEFORE USE.

Sterile. Spray dried. Preservative Free.

*Each single-dose vial contains:

Vancomycin hydrochloride equivalent to 500 mg vancomycin.

Recommended Dosage: See prescribing information. Reconstitute with 10 mL Sterile Water for Injection. The resultant solution will contain vancomycin 50 mg/mL.

AFTER RECONSTITUTION, FURTHER DILUTION IS REQUIRED.

Prior to reconstitution, store at 20ºC to 25ºC (68ºF to 77ºF) [See USP Controlled Room Temperature].

After reconstitution, this vial may be stored in a refrigerator at 2ºC to 8ºC (36ºF to 46ºF) for 96 hours without significant loss of potency.

Single-Dose Vial-Discard Unused Portion.

Manufactured by:

Zhejiang Novus Pharmaceuticals Co., Ltd.,

No. 125, Yuezhong Rd, Lihai Subdistrict,

Yuecheng District, Shaoxing, 312366,

Zhejiang, China

Distributed by:

Hikma Pharmaceuticals USA Inc.

Berkeley Heights, NJ 07922

hikma.

Rev. 5/2024

Vial Label

NDC 0143-9161-01

Rx only

Vancomycin Hydrochloride

for Injection

Equivalent to

500 mg*/ vial

Vancomycin

For Oral Use, see prescribing information.

For Intravenous Use

After Reconstitution Must Be Further Diluted Before Use

READ INSERT FOR PRECAUTIONS AND DIRECTIONS BEFORE USE.

Sterile. Spray dried. Preservative Free.

*Each single-dose vial contains: Vancomycin hydrochloride equivalent to 500 mg vancomycin.

Recommended Dosage: See prescribing information. Reconstitute contents with 10 mL Sterile Water for Injection. The resultant solution will contain vancomycin 50 mg/mL. AFTER RECONSTITUTION, FURTHER DILUTION IS REQUIRED.

Prior to reconstitution, store at 20ºC to 25ºC (68ºF to 77ºF) [See USP Controlled Room Temperature]. After reconstitution, this vial may be stored in a refrigerator at 2ºC to 8ºC (36ºF to 46ºF) for 96 hours without significant loss of potency.

Single-Dose Vial-Discard Unused Portion.

Manufactured by:

Zhejiang Novus Pharmaceuticals Co., Ltd.,

No. 125, Yuezhong Rd, Lihai Subdistrict, Yuecheng

District, Shaoxing, 312366, Zhejiang, China

Distributed by:

Hikma Pharmaceuticals USA Inc.

Berkeley Heights, NJ 07922

Rev. 3/2023

Lot

Exp YYYY-MM-DD

Package Label - NDC 0143-9161-25 - NDC 0143-9161-01

Carton Label

NDC 0143-9161-25

Rx Only

Vancomycin Hydrochloride

for Injection

Equivalent to

500 mg*/ vial

Vancomycin

25 Vials

For Oral Use, see prescribing information.

For Intravenous Use

After Reconstitution Must Be Further Diluted Before Use

READ INSERT FOR PRECAUTIONS AND DIRECTIONS BEFORE USE.

Sterile. Spray dried. Preservative Free.

*Each single-dose vial contains:

Vancomycin hydrochloride equivalent to 500 mg vancomycin.

Recommended Dosage: See prescribing information. Reconstitute with 10 mL Sterile Water for Injection. The resultant solution will contain vancomycin 50 mg/mL.

AFTER RECONSTITUTION, FURTHER DILUTION IS REQUIRED.

Prior to reconstitution, store at 20ºC to 25ºC (68ºF to 77ºF) [See USP Controlled Room Temperature].

After reconstitution, this vial may be stored in a refrigerator at 2ºC to 8ºC (36ºF to 46ºF) for 96 hours without significant loss of potency.

Single-Dose Vial-Discard Unused Portion.

Manufactured by:

Zhejiang Novus Pharmaceuticals Co., Ltd.,

No. 125, Yuezhong Rd, Lihai Subdistrict,

Yuecheng District, Shaoxing, 312366,

Zhejiang, China

Distributed by:

Hikma Pharmaceuticals USA Inc.

Berkeley Heights, NJ 07922

hikma.

Rev. 5/2024

Vial Label

NDC 0143-9161-01

Rx only

Vancomycin Hydrochloride

for Injection

Equivalent to

500 mg*/ vial

Vancomycin

For Oral Use, see prescribing information.

For Intravenous Use

After Reconstitution Must Be Further Diluted Before Use

READ INSERT FOR PRECAUTIONS AND DIRECTIONS BEFORE USE.

Sterile. Spray dried. Preservative Free.

*Each single-dose vial contains: Vancomycin hydrochloride equivalent to 500 mg vancomycin.

Recommended Dosage: See prescribing information. Reconstitute contents with 10 mL Sterile Water for Injection. The resultant solution will contain vancomycin 50 mg/mL. AFTER RECONSTITUTION, FURTHER DILUTION IS REQUIRED.

Prior to reconstitution, store at 20ºC to 25ºC (68ºF to 77ºF) [See USP Controlled Room Temperature]. After reconstitution, this vial may be stored in a refrigerator at 2ºC to 8ºC (36ºF to 46ºF) for 96 hours without significant loss of potency.

Single-Dose Vial-Discard Unused Portion.

Manufactured by:

Zhejiang Novus Pharmaceuticals Co., Ltd.,

No. 125, Yuezhong Rd, Lihai Subdistrict, Yuecheng

District, Shaoxing, 312366, Zhejiang, China

Distributed by:

Hikma Pharmaceuticals USA Inc.

Berkeley Heights, NJ 07922

Rev. 3/2023

Lot

Exp YYYY-MM-DD

Package Label - NDC 0143-9473-10 - NDC 0143-9473-01

Carton Label

NDC 0143-9473-10

Rx Only

Vancomycin Hydrochloride

for Injection

Equivalent to

750 mg*/ vial

Vancomycin

10 Vials

For Oral Use, see prescribing information.

For Intravenous Use

After Reconstitution Must Be Further Diluted Before Use

READ INSERT FOR PRECAUTIONS AND DIRECTIONS BEFORE USE.

Sterile. Spray dried. Preservative Free.

*Each single-dose vial contains:

Vancomycin hydrochloride equivalent to 750 mg vancomycin.

Recommended Dosage: See prescribing information. Reconstitute with 15 mL Sterile Water for Injection. The resultant solution will contain vancomycin 50 mg/mL.

AFTER RECONSTITUTION, FURTHER DILUTION IS REQUIRED.

Prior to reconstitution, store at 20ºC to 25ºC (68ºF to 77ºF) [See USP Controlled Room Temperature].

After reconstitution, this vial may be stored in a refrigerator at 2ºC to 8ºC (36ºF to 46ºF) for 96 hours without significant loss of potency.

Single-Dose Vial-Discard Unused Portion.

Manufactured by:

Zhejiang Novus Pharmaceuticals Co., Ltd.,

No. 125, Yuezhong Rd, Lihai Subdistrict,

Yuecheng District, Shaoxing, 312366,

Zhejiang, China

Distributed by:

Hikma Pharmaceuticals USA Inc.

Berkeley Heights, NJ 07922

hikma.

Rev. 8/2025

Vial Label

NDC 0143-9473-01

Rx only

Vancomycin Hydrochloride

for Injection

Equivalent to

750 mg*/ vial

Vancomycin

For Oral Use, see prescribing information.

For Intravenous Use

After Reconstitution Must Be Further Diluted Before Use

READ INSERT FOR PRECAUTIONS AND DIRECTIONS BEFORE USE.

Sterile. Spray dried. Preservative Free.

*Each single-dose vial contains: Vancomycin hydrochloride equivalent to 750 mg vancomycin.

Recommended Dosage: See prescribing information. Reconstitute contents with 15 mL Sterile Water for Injection. The resultant solution will contain vancomycin 50 mg/mL. AFTER RECONSTITUTION, FURTHER DILUTION IS REQUIRED.

Prior to reconstitution, store at 20ºC to 25ºC (68ºF to 77ºF) [See USP Controlled Room Temperature]. After reconstitution, this vial may be stored in a refrigerator at 2ºC to 8ºC (36ºF to 46ºF) for 96 hours without significant loss of potency.

Single-Dose Vial-Discard Unused Portion.

Manufactured by:

Zhejiang Novus Pharmaceuticals Co., Ltd.,

No. 125, Yuezhong Rd, Lihai Subdistrict, Yuecheng

District, Shaoxing, 312366, Zhejiang, China

Distributed by:

Hikma Pharmaceuticals USA Inc.

Berkeley Heights, NJ 07922

Rev. 8/2025

Lot

Exp YYYY-MM-DD

Package Label - NDC 0143-9162-10 - NDC 0143-9162-01

Carton Label

NDC 0143-9162-10

Rx Only

Vancomycin Hydrochloride

for Injection

Equivalent to

1 g*/ vial

Vancomycin

10 Vials

For Oral Use, see prescribing information.

For Intravenous Use

After Reconstitution Must Be Further Diluted Before Use

READ INSERT FOR PRECAUTIONS AND DIRECTIONS BEFORE USE.

Sterile. Spray dried. Preservative Free.

*Each single-dose vial contains:

Vancomycin hydrochloride equivalent to 1 g vancomycin.

Recommended Dosage: See prescribing information. Reconstitute with 20 mL Sterile Water for Injection. The resultant solution will contain vancomycin 50 mg/mL.

AFTER RECONSTITUTION, FURTHER DILUTION IS REQUIRED.

Prior to reconstitution, store at 20ºC to 25ºC (68ºF to 77ºF) [See USP Controlled Room Temperature].

After reconstitution, this vial may be stored in a refrigerator at 2ºC to 8ºC (36ºF to 46ºF) for 96 hours without significant loss of potency.

Single-Dose Vial-Discard Unused Portion.

Manufactured by:

Zhejiang Novus Pharmaceuticals Co., Ltd.,

No. 125, Yuezhong Rd, Lihai Subdistrict,

Yuecheng District, Shaoxing, 312366,

Zhejiang, China

Distributed by:

Hikma Pharmaceuticals USA Inc.

Berkeley Heights, NJ 07922

hikma.

Rev. 5/2024

Vial Label

NDC 0143-9162-01

Rx only

Vancomycin Hydrochloride

for Injection

Equivalent to

1 g*/ vial

Vancomycin

For Oral Use, see prescribing information.

For Intravenous Use

After Reconstitution Must Be Further Diluted Before Use

READ INSERT FOR PRECAUTIONS AND DIRECTIONS BEFORE USE.

Sterile. Spray dried. Preservative Free.

*Each single-dose vial contains: Vancomycin hydrochloride equivalent to 1 g vancomycin.

Recommended Dosage: See prescribing information. Reconstitute contents with 20 mL Sterile Water for Injection. The resultant solution will contain vancomycin 50 mg/mL. AFTER RECONSTITUTION, FURTHER DILUTION IS REQUIRED.

Prior to reconstitution, store at 20ºC to 25ºC (68ºF to 77ºF) [See USP Controlled Room Temperature]. After reconstitution, this vial may be stored in a refrigerator at 2ºC to 8ºC (36ºF to 46ºF) for 96 hours without significant loss of potency.

Single-Dose Vial-Discard Unused Portion.

Manufactured by:

Zhejiang Novus Pharmaceuticals Co., Ltd.,

No. 125, Yuezhong Rd, Lihai Subdistrict, Yuecheng

District, Shaoxing, 312366, Zhejiang, China

Distributed by:

Hikma Pharmaceuticals USA Inc.

Berkeley Heights, NJ 07922

Rev. 3/2023

Lot

Exp YYYY-MM-DD

Package Label - NDC 0143-9474-10 - NDC 0143-9474-01

Carton Label

NDC 0143-9474-10

Rx Only

Vancomycin Hydrochloride

for Injection

Equivalent to

1.25 g*/ vial

Vancomycin

10 Vials

For Oral Use, see prescribing information.

For Intravenous Use

After Reconstitution Must Be Further Diluted Before Use

READ INSERT FOR PRECAUTIONS AND DIRECTIONS BEFORE USE.

Sterile. Spray dried. Preservative Free.

*Each single-dose vial contains:

Vancomycin hydrochloride equivalent to 1.25 g vancomycin.

Recommended Dosage: See prescribing information. Reconstitute with 25 mL Sterile Water for Injection. The resultant solution will contain vancomycin 50 mg/mL.

AFTER RECONSTITUTION, FURTHER DILUTION IS REQUIRED.

Prior to reconstitution, store at 20ºC to 25ºC (68ºF to 77ºF) [See USP Controlled Room Temperature].

After reconstitution, this vial may be stored in a refrigerator at 2ºC to 8ºC (36ºF to 46ºF) for 96 hours without significant loss of potency.

Single-Dose Vial-Discard Unused Portion.

Manufactured by:

Zhejiang Novus Pharmaceuticals Co., Ltd.,

No. 125, Yuezhong Rd, Lihai Subdistrict,

Yuecheng District, Shaoxing, 312366,

Zhejiang, China

Distributed by:

Hikma Pharmaceuticals USA Inc.

Berkeley Heights, NJ 07922

hikma.

Rev. 8/2025

Vial Label

NDC 0143-9474-01

Rx only

Vancomycin Hydrochloride

for Injection

Equivalent to

1.25 g*/ vial

Vancomycin

For Oral Use, see prescribing information.

For Intravenous Use

After Reconstitution Must Be Further Diluted Before Use

READ INSERT FOR PRECAUTIONS AND DIRECTIONS BEFORE USE.

Sterile. Spray dried. Preservative Free.

*Each single-dose vial contains: Vancomycin hydrochloride equivalent to 1.25 g vancomycin.

Recommended Dosage: See prescribing information. Reconstitute contents with 25 mL Sterile Water for Injection. The resultant solution will contain vancomycin 50 mg/mL. AFTER RECONSTITUTION, FURTHER DILUTION IS REQUIRED.

Prior to reconstitution, store at 20ºC to 25ºC (68ºF to 77ºF) [See USP Controlled Room Temperature]. After reconstitution, this vial may be stored in a refrigerator at 2ºC to 8ºC (36ºF to 46ºF) for 96 hours without significant loss of potency.

Single-Dose Vial-Discard Unused Portion.

Manufactured by:

Zhejiang Novus Pharmaceuticals Co., Ltd.,

No. 125, Yuezhong Rd, Lihai Subdistrict, Yuecheng

District, Shaoxing, 312366, Zhejiang, China

Distributed by:

Hikma Pharmaceuticals USA Inc.

Berkeley Heights, NJ 07922

Rev. 8/2025

Lot

Exp YYYY-MM-DD

Package Label - NDC 0143-9475-10 - NDC 0143-9475-01

Carton Label

NDC 0143-9475-10

Rx Only

Vancomycin Hydrochloride

for Injection

Equivalent to

1.5 g*/ vial

Vancomycin

10 Vials

For Oral Use, see prescribing information.

For Intravenous Use

After Reconstitution Must Be Further Diluted Before Use

READ INSERT FOR PRECAUTIONS AND DIRECTIONS BEFORE USE.

Sterile. Spray dried. Preservative Free.

*Each single-dose vial contains:

Vancomycin hydrochloride equivalent to 1.5 g vancomycin.

Recommended Dosage: See prescribing information. Reconstitute with 30 mL Sterile Water for Injection. The resultant solution will contain vancomycin 50 mg/mL.

AFTER RECONSTITUTION, FURTHER DILUTION IS REQUIRED.

Prior to reconstitution, store at 20ºC to 25ºC (68ºF to 77ºF) [See USP Controlled Room Temperature].

After reconstitution, this vial may be stored in a refrigerator at 2ºC to 8ºC (36ºF to 46ºF) for 96 hours without significant loss of potency.

Single-Dose Vial-Discard Unused Portion.

Manufactured by:

Zhejiang Novus Pharmaceuticals Co., Ltd.,

No. 125, Yuezhong Rd, Lihai Subdistrict,

Yuecheng District, Shaoxing, 312366,

Zhejiang, China

Distributed by:

Hikma Pharmaceuticals USA Inc.

Berkeley Heights, NJ 07922

hikma.

Rev. 8/2025

Vial Label

NDC 0143-9475-01

Rx only

Vancomycin Hydrochloride

for Injection

Equivalent to

1.5 g*/ vial

Vancomycin

For Oral Use, see prescribing information.

For Intravenous Use

After Reconstitution Must Be Further Diluted Before Use

READ INSERT FOR PRECAUTIONS AND DIRECTIONS BEFORE USE.

Sterile. Spray dried. Preservative Free.

*Each single-dose vial contains: Vancomycin hydrochloride equivalent to 1.5 g vancomycin.

Recommended Dosage: See prescribing information. Reconstitute contents with 30 mL Sterile Water for Injection. The resultant solution will contain vancomycin 50 mg/mL. AFTER RECONSTITUTION, FURTHER DILUTION IS REQUIRED.

Prior to reconstitution, store at 20ºC to 25ºC (68ºF to 77ºF) [See USP Controlled Room Temperature]. After reconstitution, this vial may be stored in a refrigerator at 2ºC to 8ºC (36ºF to 46ºF) for 96 hours without significant loss of potency.

Single-Dose Vial-Discard Unused Portion.

Manufactured by:

Zhejiang Novus Pharmaceuticals Co., Ltd.,

No. 125, Yuezhong Rd, Lihai Subdistrict, Yuecheng

District, Shaoxing, 312366, Zhejiang, China

Distributed by:

Hikma Pharmaceuticals USA Inc.

Berkeley Heights, NJ 07922

Rev. 8/2025

Lot

Exp YYYY-MM-DD